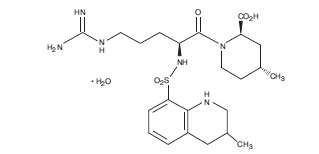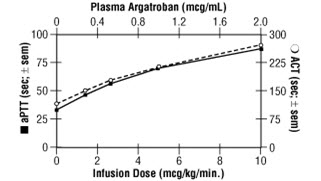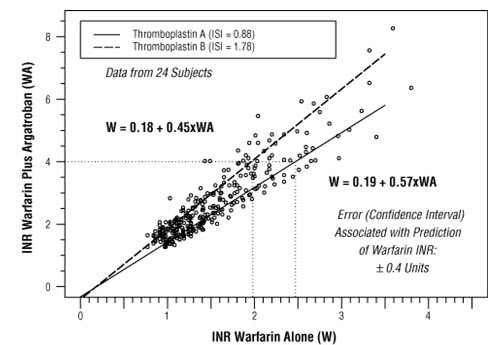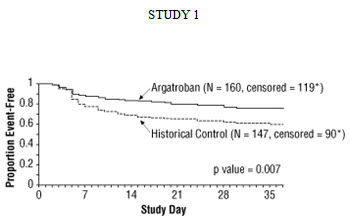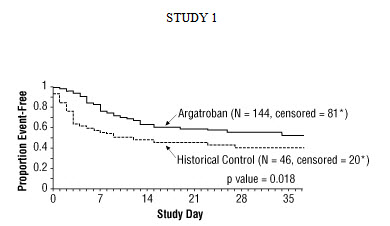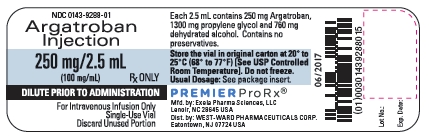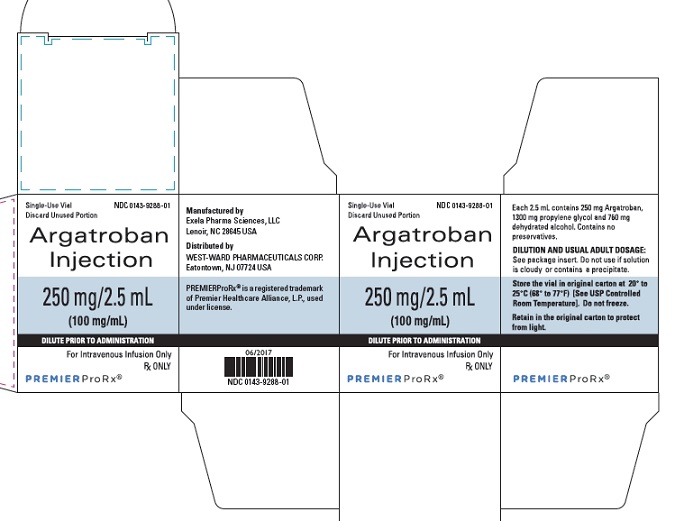 DRUG LABEL: Argatroban
NDC: 0143-9288 | Form: INJECTION
Manufacturer: Hikma Pharmaceuticals USA Inc.
Category: prescription | Type: HUMAN PRESCRIPTION DRUG LABEL
Date: 20240411

ACTIVE INGREDIENTS: ARGATROBAN 250 mg/2.5 mL
INACTIVE INGREDIENTS: PROPYLENE GLYCOL; ALCOHOL

HIGHLIGHTS OF PRESCRIBING INFORMATION

These highlights do not include all the information needed to use ARGATROBAN INJECTION safely and effectively. See full prescribing information for ARGATROBAN INJECTION.
ARGATROBAN INJECTION, for intravenous infusion only
Initial U.S. Approval: 2000

1 INDICATIONS AND USAGE

Argatroban is a direct thrombin inhibitor indicated:

- For prophylaxis or treatment of thrombosis in adult patients with heparin-induced thrombocytopenia (HIT) (1.1)
- As an anticoagulant in adult patients with or at risk for HIT undergoing percutaneous coronary intervention (PCI) (1.2)

2 DOSAGE AND ADMINISTRATION

- Argatroban Injection 250 mg/2.5 mL (100 mg/mL) must be diluted 100-fold by mixing with 0.9% Sodium Chloride Injection, 5% Dextrose Injection, or Lactated Ringer’s Injection to a final concentration of 1 mg/mL. (2.1)

Heparin-Induced Thrombocytopenia
The dose for heparin-induced thrombocytopenia without hepatic impairment is 2 mcg/kg/min administered as a continuous infusion. (2.2)

Percutaneous Coronary Intervention
The dose for patients with or at risk for heparin-induced thrombocytopenia undergoing percutaneous coronary intervention is started at 25 mcg/kg/min and a bolus of 350 mcg/kg administered via a large bore intravenous line over 3 to 5 minutes. (2.3)

3 DOSAGE FORMS AND STRENGTHS

- Injection: 250 mg/2.5 mL (100 mg/mL) single-dose vial. (3)

4 CONTRAINDICATIONS

- Major bleeding (4)
- History of hypersensitivity to this product (4)

5 WARNINGS AND PRECAUTIONS

- Hemorrhage can occur. Unexplained fall in hematocrit or blood pressure may indicate hemorrhage, (5.1)
- Hepatic impairment: Adjust starting dose and titrate carefully in patients with HIT who have moderate or severe hepatic impairment. Avoid use in PCI in patients with clinically significant hepatic impairment. (5.2)

6 ADVERSE REACTIONS

- HIT patients: The most common (>5%) adverse reactions were dyspnea, hypotension, fever, diarrhea, sepsis, and cardiac arrest. (6.1)
- PCI patients: The most common (>5%) adverse reactions were chest pain, hypotension, back pain, nausea, vomiting and headache. (6.1)

To report SUSPECTED ADVERSE REACTIONS, contact Hikma Pharmaceuticals USA Inc. at 1-877-233-2001 or FDA at 1-800-FDA-1088 or www.fda.gov/medwatch.

7 DRUG INTERACTIONS

- Heparin: Allow sufficient time for heparin’s effect on activated partial thromboplastin time (aPTT) to decrease before initiating Argatroban Injection therapy. (7.1)
- Warfarin: Concomitant use results in increased prolongation of PT and INR. (7.2)
- Thrombolytic agents or glycoprotein IIb/IIIa antagonists: Safety and effectiveness of concomitant use with argatroban have not been established. (7.4, 7.5)

8 USE IN SPECIFIC POPULATIONS

- Lactation: Discontinue nursing or drug, taking into account the importance of the drug to the mother. (8.2)
- Pediatric Use: Safety and effectiveness have not been established. (8.4)

FULL PRESCRIBING INFORMATION

1 INDICATIONS AND USAGE

1.1 Heparin-Induced Thrombocytopenia

Argatroban Injection is indicated for prophylaxis or treatment of thrombosis in adult patients with heparin-induced thrombocytopenia (HIT).

1.2 Percutaneous Coronary Intervention

Argatroban Injection is indicated as an anticoagulant in adult patients with or at risk for HIT undergoing percutaneous coronary intervention (PCI).

2 DOSAGE AND ADMINISTRATION

2.1 Preparation for Intravenous Administration

Argatroban Injection 250 mg/2.5 mL (100 mg/mL) must be diluted 100-fold prior to infusion. Argatroban should not be mixed with other drugs prior to dilution.

Argatroban Injection 250 mg/2.5 mL (100 mg/mL)

Argatroban 250 mg/2.5 mL (100 mg/mL) should be diluted in 0.9% Sodium Chloride Injection, 5% Dextrose Injection, or Lactated Ringer’s Injection to a final concentration of 1 mg/mL. The contents of each 2.5-mL vial should be diluted 100-fold by mixing with 250 mL of diluent. Use 250 mg (2.5 mL) per 250 mL of diluent or 500 mg (5 mL) per 500 mL of diluent.

The constituted solution must be mixed by repeated inversion of the diluent bag for 1 minute. Upon preparation, the solution may show slight but brief haziness due to the formation of microprecipitates that rapidly dissolve upon mixing. Use of diluent at room temperature is recommended. Colder temperatures can slow down the rate of dissolution of precipitates. The final solution must be clear before use. The pH of the intravenous solution prepared as recommended is 3.2 to 7.5. Solutions prepared as recommended are stable at controlled room temperature, 20º to 25ºC (68º to 77ºF) (see USP) in ambient indoor light for 24 hours; therefore, light-resistant measures such as foil protection for intravenous lines are unnecessary. Solutions are physically and chemically stable for up to 96 hours when protected from light and stored at controlled room temperature, 20º to 25ºC (68º to 77ºF) (see USP) or at refrigerated conditions, 5º±3ºC (41º±5ºF). Prepared solutions should not be exposed to direct sunlight. No significant potency losses have been noted following simulated delivery of the solution through intravenous tubing.

Parenteral drug products should be inspected visually for particulate matter and discoloration prior to administration whenever solution and container permit.

2.2 Dosing in Patients with Heparin-Induced Thrombocytopenia

Initial Dosage

Before administering argatroban, discontinue heparin therapy and obtain a baseline activated partial thromboplastin time (aPTT). The recommended initial dose of argatroban for adult patients without hepatic impairment is 2 mcg/kg/min, administered as a continuous infusion (see Table 1).

Table 1
Recommended Doses and Infusion Rates for 2 mcg/kg/min Dose of Argatroban for Patients With HIT* and Without Hepatic Impairment (1 mg/mL Final Concentration)
Body Weight (kg) | Dose (mcg/min) | Infusion Rate (mL/hr)
50 | 100 | 6
60 | 120 | 7
70 | 140 | 8
80 | 160 | 10
90 | 180 | 11
100 | 200 | 12
110 | 220 | 13
120 | 240 | 14
130 | 260 | 16
140 | 280 | 17

*with or without thrombosis

Monitoring Therapy
For use in HIT, therapy with Argatroban Injection is monitored using the aPTT with a target range of 1.5 to 3 times the initial baseline value (not to exceed 100 seconds). Tests of anticoagulant effects (including the aPTT) typically attain steady-state levels within 1 to 3 hours following initiation of Argatroban Injection.

Check the aPTT 2 hours after initiation of therapy and after any dose change to confirm that the patient has attained the desired therapeutic range.

Dosage Adjustment
After the initiation of Argatroban Injection, adjust the dose (not to exceed 10 mcg/kg/min) as necessary to obtain a steady-state aPTT in the target range [see Clinical Studies (14.1)].

2.3 Dosing in Patients Undergoing Percutaneous Coronary Intervention

Initial Dosage
Initiate an infusion of Argatroban Injection at 25 mcg/kg/min and administer a bolus of 350 mcg/kg via a large bore intravenous line over 3 to 5 minutes (see Table 2). Check an activated clotting time (ACT) 5 to 10 minutes after the bolus dose is completed. The PCI procedure may proceed if the ACT is greater than 300 seconds.

Dosage Adjustment
If the ACT is less than 300 seconds, an additional intravenous bolus dose of 150 mcg/kg should be administered, the infusion dose increased to 30 mcg/kg/min, and the ACT checked 5 to 10 minutes later (see Table 3).

If the ACT is greater than 450 seconds, decrease the infusion rate to 15 mcg/kg/min, and check the ACT 5 to 10 minutes later (Table 3).

Continue titrating the dose until a therapeutic ACT (between 300 and 450 seconds) has been achieved; continue the same infusion rate for the duration of the PCI procedure.

In case of dissection, impending abrupt closure, thrombus formation during the procedure, or inability to achieve or maintain an ACT over 300 seconds, additional bolus doses of 150 mcg/kg may be administered and the infusion dose increased to 40 mcg/kg/min. Check the ACT after each additional bolus or change in the rate of infusion.

Table 2
Recommended Starting and Maintenance Doses (Within the Target ACT Range) of Argatroban Injection in Patients Undergoing PCI Without Hepatic Impairment (1 mg/mL Final Concentration)
Body Weight (kg) | Starting Bolus Dose; (350 mcg/kg) |  | Starting and Maintenance Continuous Infusion Dosing For ACT 300-450 seconds 25 mcg/kg/min
Body Weight (kg) | Bolus Dose (mcg) | Bolus Volume (mL) | Continuous Infusion Dose (mcg/min) | Continuous Infusion Rate (mL/hr)
50 | 17500 | 18 | 1250 | 75
60 | 21000 | 21 | 1500 | 90
70 | 24500 | 25 | 1750 | 105
80 | 28000 | 28 | 2000 | 120
90 | 31500 | 32 | 2250 | 135
100 | 35000 | 35 | 2500 | 150
110 | 38500 | 39 | 2750 | 165
120 | 42000 | 42 | 3000 | 180
130 | 45500 | 46 | 3250 | 195
140 | 49000 | 49 | 3500 | 210

NOTE: 1 mg = 1000 mcg; 1 kg = 2.2 lbs

Table 3
Recommended Dose Adjustments of Argatroban Injection for Patients Outside of ACT Target Range Undergoing PCI Without Hepatic Impairment (1 mg/mL Final Concentration)
Body Weight (kg) | If ACT Less than 300 seconds Dosage Adjustment† 30 mcg/kg/min |  |  |  | If ACT Greater than 450 seconds Dosage Adjustment* 15 mcg/kg/min
Body Weight (kg) | Additional Bolus Dose (mcg) | Bolus Volume (mL) | Continuous Infusion Dose (mcg/min) | Continuous Infusion Rate (mL/hr) | Continuous Infusion Dose (mcg/min) | Continuous Infusion Rate (mL/hr)
50 | 7500 | 8 | 1500 | 90 | 750 | 45
60 | 9000 | 9 | 1800 | 108 | 900 | 54
70 | 10500 | 11 | 2100 | 126 | 1050 | 63
80 | 12000 | 12 | 2400 | 144 | 1200 | 72
90 | 13500 | 14 | 2700 | 162 | 1350 | 81
100 | 15000 | 15 | 3000 | 180 | 1500 | 90
110 | 16500 | 17 | 3300 | 198 | 1650 | 99
120 | 18000 | 18 | 3600 | 216 | 1800 | 108
130 | 19500 | 20 | 3900 | 234 | 1950 | 117
140 | 21000 | 21 | 4200 | 252 | 2100 | 126

NOTE: 1 mg = 1000 mcg; 1 kg = 2.2 lbs
†Additional intravenous bolus dose of 150 mcg/kg should be administered if ACT less than 300 seconds.
* No bolus dose is given if ACT greater than 450 seconds

Monitoring Therapy
For use in PCI, therapy with Argatroban Injection is monitored using ACT. Obtain ACTs before dosing, 5 to 10 minutes after bolus dosing, following adjustments in the infusion rate, and at the end of the PCI procedure. Obtain additional ACTs every 20 to 30 minutes during prolonged procedure.

Continued Anticoagulation after PCI
If a patient requires anticoagulation after the procedure, Argatroban Injection may be continued, but at a rate of 2 mcg/kg/min and adjusted as needed to maintain the aPTT in the desired range [see Dosage and Administration (2.1)].

2.4 Dosing in Patients with Hepatic Impairment

Initial Dosage

For adult patients with HIT and moderate or severe hepatic impairment (based on Child-Pugh classification), an initial dose of 0.5 mcg/kg/min is recommended, based on the approximately 4-fold decrease in argatroban clearance relative to those with normal hepatic function. Monitor the aPTT closely, and adjust the dosage as clinically indicated.

Monitoring Therapy
Achievement of steady state aPTT levels may take longer and require more dose adjustments in patients with hepatic impairment compared to patients with normal hepatic function.

For patients with hepatic impairment undergoing PCI and who have HIT or are at risk for HIT, carefully titrate argatroban until the desired level of anticoagulation is achieved. Use of argatroban in PCI patients with clinically significant hepatic disease or AST/ALT levels ≥3 times the upper limit of normal should be avoided [see Warnings and Precautions (5.2)].

2.5 Conversion to Oral Anticoagulant Therapy

Initiating Oral Anticoagulant Therapy
When converting patients from argatroban to oral anticoagulant therapy, consider the potential for combined effects on INR with co-administration of argatroban and warfarin. A loading dose of warfarin should not be used. Initiate therapy using the expected daily dose of warfarin. To avoid prothrombotic effects and to ensure continuous anticoagulation when initiating warfarin, it is suggested that argatroban and warfarin therapy be overlapped. There are insufficient data available to recommend the duration of the overlap.

Co-Administration of Warfarin and Argatroban Injection at Doses up to 2 mcg/kg/min
Measure INR daily while Argatroban Injection and warfarin are co-administered. In general, with doses of Argatroban Injection up to 2 mcg/kg/min, Argatroban Injection can be discontinued when the INR is >4 on combined therapy. After Argatroban Injection is discontinued, repeat the INR measurement in 4 to 6 hours. If the repeat INR is below the desired therapeutic range, resume the infusion of Argatroban Injection and repeat the procedure daily until the desired therapeutic range on warfarin alone is reached.

Co-Administration of Warfarin and Argatroban Injection at Doses Greater than 2 mcg/kg/min
For doses of argatroban greater than 2 mcg/kg/min, the relationship of INR between warfarin alone to the INR on warfarin plus argatroban is less predictable. In this case, in order to predict the INR on warfarin alone, temporarily reduce the dose of Argatroban Injection to a dose of 2 mcg/kg/min. Repeat the INR on Argatroban Injection and warfarin 4 to 6 hours after reduction of the Argatroban Injection dose and follow the process outlined above for administering Argatroban Injection at doses up to 2 mcg/kg/min.

3 DOSAGE FORMS AND STRENGTHS

- Injection: 250 mg/2.5 mL (100 mg/mL) single-dose vial

4 CONTRAINDICATIONS

Argatroban is contraindicated in:

- Patients with major bleeding, [see Warnings and Precautions (5.1)]
- Patients with a history of hypersensitivity to argatroban. Airway, skin, and generalized hypersensitivity reactions have been reported [see Adverse Reactions (6.1)]

5 WARNINGS AND PRECAUTIONS

5.1 Risk of Hemorrhage

Hemorrhage can occur at any site in the body in patients receiving argatroban. Unexplained fall in hematocrit or blood pressure may indicate hemorrhage. Intracranial and retroperitoneal hemorrhage [see Adverse Reactions (6.1)] have been reported. The risk of hemorrhage with argatroban may be increased in severe hypertension; immediately following lumbar puncture, spinal anesthesia, major surgery (especially involving the brain, spinal cord, or eye), hematologic conditions associated with increased bleeding tendencies such as congenital or acquired bleeding disorders, and gastrointestinal lesions such as ulcerations.

Concomitant use of argatroban with antiplatelet agents, thrombolytics, and other anticoagulants may increase the risk of bleeding.

5.2 Use in Hepatic Impairment

When administering argatroban to patients with hepatic impairment, start with a lower dose and carefully titrate until the desired level of anticoagulation is achieved. Achievement of steady state aPTT levels may take longer and require more argatroban dose adjustments in patients with hepatic impairment compared to patients with normal hepatic function [see Use in Specific Populations (8.6)]. Also, upon cessation of argatroban infusion in the hepatically impaired patient, full reversal of anticoagulant effects may require longer than 4 hours due to decreased clearance and increased elimination half-life of argatroban [see Dosage and Administration (2.4), Clinical Pharmacology (12.3)]. Avoid the use of high doses of argatroban in patients undergoing PCI who have clinically significant hepatic disease or AST/ALT levels ≥3 times the upper limit of normal.

5.3 Laboratory Tests

Anticoagulation effects associated with argatroban infusion at doses up to 40 mcg/kg/min correlate with increases of the aPTT. Although other global clot-based tests including prothrombin time (PT), the International Normalized Ratio (INR), and thrombin time (TT) are affected by argatroban, the therapeutic ranges for these tests have not been identified for argatroban therapy. In clinical trials in PCI, the ACT was used for monitoring argatroban anticoagulant activity during the procedure. The concomitant use of argatroban and warfarin results in prolongation of the PT and INR beyond that produced by warfarin alone [see Dosage and Administration (2.5), Clinical Pharmacology (12.2)].

6 ADVERSE REACTIONS

The following adverse reaction is also discussed in other sections of the labeling:

- Risk of Hemorrhage [see Warnings and Precautions (5.1)].

6.1 Clinical Trials Experience

Adverse Reactions in Patients with HIT (With or Without Thrombosis)

Because clinical trials are conducted under widely varying conditions, adverse reaction rates observed in the clinical trials of a drug cannot be directly compared to rates in the clinical trials of another drug and may not reflect the rates observed in practice.

The following safety information is based on all 568 patients treated with argatroban in Study 1 and Study 2. The safety profile of the patients from these studies is compared with that of 193 historical controls in which the adverse reactions were collected retrospectively. Adverse reactions are separated into hemorrhagic and non-hemorrhagic reactions.

Major bleeding was defined as bleeding that was overt and associated with a hemoglobin decrease ≥ 2 g/dL, that led to a transfusion of ≥ 2 units, or that was intracranial, retroperitoneal, or into a major prosthetic joint. Minor bleeding was overt bleeding that did not meet the criteria for major bleeding.

Table 4 gives an overview of the most frequently observed hemorrhagic reactions, presented separately by major and minor bleeding, sorted by decreasing occurrence among argatroban-treated patients with HIT (with or without thrombosis).

Table 4
Major and Minor Hemorrhagic Adverse Reactions in Patients With HIT*
Major Hemorrhagic Reactionsa
 | Argatroban-treated Patients (Study 1 and Study 2) (n = 568) % | Historical Controlc (n = 193) %
Overall bleeding | 5.3 | 6.7
Gastrointestinal | 2.3 | 1.6
Genitourinary and hematuria | 0.9 | 0.5
Decrease in hemoglobin and hematocrit | 0.7 | 0
Multisystem hemorrhage and DIC | 0.5 | 1
Limb and BKA stump | 0.5 | 0
Intracranial hemorrhage | 0b | 0.5
Minor Hemorrhagic Reactionsa
 | Argatroban-treated Patients (Study 1 and Study 2); (n = 568) % | Historical Controlc (n = 193) %
Gastrointestinal | 14.4 | 18.1
Genitourinary and hematuria | 11.6 | 0.8
Decrease in hemoglobin and hematocrit | 10.4 | 0
Groin | 5.4 | 3.1
Hemoptysis | 2.9 | 0.8
Brachial | 2.4 | 0.8

* with or without thrombosis
a) Patients may have experienced more than 1 adverse reaction.
b) One patient experienced intracranial hemorrhage 4 days after discontinuation of argatroban and following therapy with urokinase and
oral anticoagulation.
c) The historical control group consisted of patients with a clinical diagnosis of HIT (with or without thrombosis) that were considered eligible by an independent medical panel.
DIC = disseminated intravascular coagulation.
BKA = below the knee amputation.

Table 5 gives an overview of the most frequently observed non-hemorrhagic reactions sorted by decreasing frequency of occurrence (≥2%) among argatroban-treated HIT/HITTS patients.

Table 5
Non-hemorrhagic Adverse Reactions in Patientsa With HITb
 | Argatroban-treated Patients (Study 1 and Study 2) (n = 568) % | Historical Controlc (n = 193) %
Dyspnea | 8.1 | 8.8
Hypotension | 7.2 | 2.6
Fever | 6.9 | 2.1
Diarrhea | 6.2 | 1.6
Sepsis | 6.0 | 12.4
Cardiac arrest | 5.8 | 3.1
Nausea | 4.8 | 0.5
Ventricular tachycardia | 4.8 | 3.1
Pain | 4.6 | 3.1
Urinary tract infection | 4.6 | 5.2
Vomiting | 4.2 | 0
Infection | 3.7 | 3.6
Pneumonia | 3.3 | 9.3
Atrial fibrillation | 3.0 | 11.4
Coughing | 2.8 | 1.6
Abnormal renal function | 2.8 | 4.7
Abdominal pain | 2.6 | 1.6
Cerebrovascular disorder | 2.3 | 4.1

a) Patients may have experienced more than 1 adverse reaction.
b) With or without thrombosis
c) The historical control group consisted of patients with a clinical diagnosis of HIT (with or without thrombosis) that were considered eligible by an independent medical panel.

Adverse Reactions in Patients with or at Risk for HIT Undergoing PCI

The following safety information is based on 91 patients initially treated with argatroban and 21 patients subsequently re-exposed to argatroban for a total of 112 PCIs with argatroban anticoagulation. Adverse reactions are separated into hemorrhagic (Table 6) and non-hemorrhagic (Table 7) reactions.

Major bleeding was defined as bleeding that was overt and associated with a hemoglobin decrease ≥5 g/dL, that led to a transfusion of ≥2 units, or that was intracranial, retroperitoneal, or into a major prosthetic joint. The rate of major bleeding events in patients treated with argatroban in the PCI trials was 1.8%.

Table 6
Major and Minor Hemorrhagic Adverse Reactions in Patients With HIT Undergoing PCI
Major Hemorrhagic Reactionsa
 | Argatroban-treated Patients (n = 112)b %
Retroperitoneal | 0.9
Gastrointestinal | 0.9
Intracranial | 0
Minor Hemorrhagic Reactionsa
 | Argatroban-treated Patients (n = 112)b %
Groin (bleeding or hematoma) | 3.6
Gastrointestinal (includes hematemesis) | 2.6
Genitourinary (includes hematuria) | 1.8
Decrease in hemoglobin and/or hematocrit | 1.8
CABG (coronary arteries) | 1.8
Access site | 0.9
Hemoptysis | 0.9
Other | 0.9

a) Patients may have experienced more than 1 adverse reaction.
b) 91 patients who underwent 112 interventions.
CABG = coronary artery bypass graft.

Table 7 gives an overview of the most frequently observed non-hemorrhagic adverse reactions (>2%), sorted by decreasing frequency of occurrence among argatroban-treated PCI patients.

Table 7
Non-hemorrhagic Adverse Reactionsa in Patients With HIT Undergoing PCI
 | Argatroban Proceduresa (n = 112)b %
Chest pain | 15.2
Hypotension | 10.7
Back pain | 8.0
Nausea | 7.1
Vomiting | 6.3
Headache | 5.4
Bradycardia | 4.5
Abdominal pain | 3.6
Fever | 3.6
Myocardial infarction | 3.6

a) Patients may have experienced more than 1 adverse reaction.
b) 91 patients who underwent 112 interventions.

There were 22 serious adverse reactions in 17 PCI patients (19.6% in 112 interventions). Table 8 lists the serious adverse reactions occurring in argatroban-treated patients with or at risk for HIT undergoing PCI.

Table 8
Serious Adverse Reactions in Patients With HIT Undergoing PCIa
Coded Term | Argatroban Proceduresb (n = 112)
Myocardial infarction | 4 (3.5%)
Angina pectoris | 2 (1.8%)
Coronary thrombosis | 2 (1.8%)
Myocardial ischemia | 2 (1.8%)
Occlusion coronary | 2 (1.8%)
Chest pain | 1 (0.9%)
Fever | 1 (0.9%)
Retroperitoneal hemorrhage | 1 (0.9%)
Aortic stenosis | 1 (0.9%)
Arterial thrombosis | 1 (0.9%)
Gastrointestinal hemorrhage | 1 (0.9%)
Gastrointestinal disorder (GERD) | 1 (0.9%)
Cerebrovascular disorder | 1 (0.9%)
Lung edema | 1 (0.9%)
Vascular disorder | 1 (0.9%)

a) Individual reactions may also have been reported elsewhere (see Table 6 and 7).
b) 91 patients underwent 112 procedures. Some patients may have experienced more than 1 reaction.

Intracranial Bleeding in Other Populations

Increased risks for intracranial bleeding have been observed in investigational studies of argatroban for other uses. In a study of patients with acute myocardial infarction receiving both argatroban and thrombolytic therapy (streptokinase or tissue plasminogen activator), the overall frequency of intracranial bleeding was 1% (8 out of 810 patients). Intracranial bleeding was not observed in 317 subjects or patients who did not receive concomitant thrombolysis [see Drug Interactions (7.4)].

The safety and effectiveness of argatroban for cardiac indications other than PCI in patients with HIT have not been established. Intracranial bleeding was also observed in a prospective, placebo-controlled study of argatroban in patients who had onset of acute stroke within 12 hours of study entry. Symptomatic intracranial hemorrhage was reported in 5 of 117 patients (4.3%) who received argatroban at 1 to 3 mcg/kg/min and in none of the 54 patients who received placebo. Asymptomatic intracranial hemorrhage occurred in 5 (4.3%) and 2 (3.7%) of the patients, respectively.

Allergic Reactions

One hundred fifty-six allergic reactions or suspected allergic reactions were observed in 1,127 individuals who were treated with argatroban in clinical pharmacology studies or for various clinical indications. About 95% (148/156) of these reactions occurred in patients who concomitantly received thrombolytic therapy (e.g., streptokinase) or contrast media.

Allergic reactions or suspected allergic reactions in populations other than patients with HIT (with or without thrombosis) include (in descending order of frequency):

- Airway reactions (coughing, dyspnea): 10% or more
- Skin reactions (rash, bullous eruption): 1 to <10%
- General reactions (vasodilation): 1 to 10%

Limited data are available on the potential formation of drug-related antibodies. Plasma from 12 healthy volunteers treated with argatroban over 6 days showed no evidence of neutralizing antibodies. No loss of anticoagulant activity was noted with repeated administration of argatroban to more than 40 patients.

7 DRUG INTERACTIONS

7.1 Heparin

If argatroban is to be initiated after cessation of heparin therapy, allow sufficient time for heparin’s effect on the aPTT to decrease prior to initiation of argatroban therapy.

7.2 Oral Anticoagulant Agents

Pharmacokinetic drug-drug interactions between argatroban and warfarin (7.5 mg single oral dose) have not been demonstrated. However, the concomitant use of argatroban and warfarin (5 to 7.5 mg initial oral dose, followed by 2.5 to 6 mg/day orally for 6 to 10 days) results in prolongation of the prothrombin time (PT) and International Normalized Ratio (INR) [see Dosage and Administration (2.5) and Clinical Pharmacology (12.2)].

7.3 Aspirin/Acetaminophen

No drug-drug interactions have been demonstrated between argatroban and concomitantly administered aspirin or acetaminophen [see Clinical Pharmacology (12.3)].

7.4 Thrombolytic Agents

The safety and effectiveness of argatroban with thrombolytic agents have not been established [see Adverse Reactions (6.1)].

7.5 Glycoprotein IIb/IIIa Antagonists

The safety and effectiveness of argatroban with glycoprotein IIb/IIIa antagonists have not been established.

8 USE IN SPECIFIC POPULATIONS

8.1 Pregnancy

Risk Summary

Limited data from published literature and postmarketing reports do not suggest an association between argatroban and adverse fetal developmental outcomes. There are risks to the mother associated with untreated thrombosis in pregnancy and a risk of hemorrhage in the mother and fetus associated with use of anticoagulants (see Clinical Considerations). In animal reproduction studies, there was no evidence of adverse developmental outcomes with intravenous administration of argatroban during organogenesis in rats and rabbits at doses up to 0.3- and 0.2-times, respectively, the maximum recommended human dose (MHRD) (see Data).
The estimated background risk of major birth defects and miscarriage for the indicated population is unknown. All pregnancies have a background risk of birth defect, loss, or other adverse outcomes. In the U.S. general population, the estimated background risk of major birth defects and miscarriage in clinically recognized pregnancies is 2%-4% and 15%-20%, respectively.

Clinical Considerations

Disease-Associated Maternal and/or Embryo/Fetal Risk
Pregnancy confers an increased risk for thromboembolism that is higher for women with underlying thromboembolic disease and certain high risk pregnancy conditions. Published data describe that women with a previous history of venous thrombosis are at high risk for recurrence during pregnancy.
Fetal/Neonatal Adverse Reactions
Use of anticoagulants, including argatroban, may increase the risk of bleeding in the fetus and neonate. Monitor neonates for bleeding [see Warnings and Precautions (5.1, 5.3)].
Labor or Delivery
All patients receiving anticoagulants, including pregnant women, are at risk for bleeding. Pregnant women receiving argatroban should be carefully monitored for evidence of excessive bleeding or unexpected changes in coagulation parameters [see Warnings and Precautions (5.1, 5.3)].

Data

Animal Data
Developmental studies performed in rats with argatroban at intravenous doses up to 27 mg/kg/day (0.3 times the maximum recommended human dose, based on body surface area) and in rabbits at intravenous doses up to 10.8 mg/kg/day (0.2 times the maximum recommended human dose, based on body surface area) have revealed no evidence of harm to the fetus.

8.2 Lactation

Risk Summary

There are no data on the presence of argatroban in human milk, or its effects on milk production. Argatroban is present in rat milk. The developmental and health benefits of breastfeeding should be considered along with the mother’s clinical need for argatroban and any potential adverse effects on the breastfed infant from argatroban or from the underlying maternal condition.

8.4 Pediatric Use

Safety and effectiveness have not been established in pediatric patients.

Argatroban was studied among 18 seriously ill pediatric patients who required an alternative to heparin anticoagulation. Most patients were diagnosed with HIT or suspected HIT. Age ranges of patients were <6 months, n = 8; six months to <8 years, n = 6; 8 to 16 years, n = 4. All patients had serious underlying conditions and were receiving multiple concomitant medications. Thirteen patients received argatroban solely as a continuous infusion (no bolus dose). Dosing was initiated in the majority of these 13 patients at 1 mcg/kg/min. Dosing was titrated as needed to achieve and maintain an aPTT of 1.5 to 3 times the baseline value. Most patients required multiple dose adjustments to maintain anticoagulation parameters within the desired range. During the 30-day study period, thrombotic events occurred during argatroban administration to two patients and following argatroban discontinuation in three other patients. Major bleeding occurred among two patients: one patient experienced an intracranial hemorrhage after 4 days of argatroban therapy in the setting of sepsis and thrombocytopenia and another patient experienced an intracranial hemorrhage after receiving argatroban for greater than 14 days. The study findings did not establish the safe and effective use of argatroban in pediatric patients and the dosing of 1 mcg/kg/min was not supported by the pharmacokinetic data described below.

Pediatric Pharmacokinetics (PK) and Pharmacodynamics (PD)

PK parameters of argatroban were characterized in population PK/PD analysis model with sparse data from 15 seriously ill pediatric patients. Argatroban clearance in these seriously ill pediatric patients (0.16 L/hr/kg) was 50% lower compared to argatroban clearance in healthy adults (0.31 L/hr/kg). Four pediatric patients with elevated bilirubin (secondary to cardiac complications or hepatic impairment) had, on average, 80% lower clearance (0.03 L/hr/kg) when compared to pediatric patients with normal bilirubin levels.

These PK/PD analysis models based on a goal of aPTT prolongation of 1.5 to 3 times the baseline value and avoidance of an aPTT >100 seconds for seriously ill pediatric patients with HIT/HITTS who require an alternative to heparin suggested the following:

- For patients with normal hepatic function, a starting infusion rate of 0.75 mcg/kg/min may have comparable aPTT responses as a starting dose of 2 mcg/kg/min in healthy adults. Additionally, based on an evaluation of aPTT every two hours, increasing the dosage by 0.1 to 0.25 mcg/kg/min could achieve additional aPTT responses.
- For patients with hepatic impairment a starting infusion rate of 0.2 mcg/kg/min with increasing dosing by increments of 0.05 mcg/kg/min may have comparable argatroban exposure as expected with adult doses.

The safety and effectiveness of argatroban with the above dosing have not been adequately assessed in pediatric patients and the safety and effectiveness of argatroban is not established in pediatric patients. In addition, the described dosage did not take into account multiple factors that could affect the dosage such as current aPTT, target aPTT, and the clinical status of the patient.

8.5 Geriatric Use

Of the total number of subjects (1340) in clinical studies of argatroban, 35% were 65 and over. In the clinical studies of adult patients with HIT (with or without thrombosis), the effectiveness of argatroban was not affected by age. No trends were observed across age groups for both aPTT and the ACT. The safety analysis did suggest that older patients had increased underlying conditions, which may predispose them to adverse reactions. The studies were not sized appropriately to detect differences in safety between age groups.

8.6 Hepatic Impairment

Dose reduction and careful titration are required when administering argatroban to patients with hepatic impairment. Reversal of anticoagulant effect may be prolonged in this population [see Dosage and Administration (2.4), Warning and Precautions (5.2), Clinical Pharmacology (12.3)].

10 OVERDOSAGE

Excessive anticoagulation, with or without bleeding, may be controlled by discontinuing argatroban or by decreasing the argatroban dose. In clinical studies, anticoagulation parameters generally returned from therapeutic levels to baseline within 2 to 4 hours after discontinuation of the drug. Reversal of anticoagulant effect may take longer in patients with hepatic impairment. No specific antidote to argatroban is available; if life-threatening bleeding occurs and excessive plasma levels of argatroban are suspected, discontinue argatroban immediately and measure aPTT and other coagulation parameters. When argatroban was administered as a continuous infusion (2 mcg/kg/min) prior to and during a 4-hour hemodialysis session, approximately 20% of argatroban was cleared through dialysis.

Single intravenous doses of argatroban at 200, 124, 150, and 200 mg/kg were lethal to mice, rats, rabbits, and dogs, respectively. The symptoms of acute toxicity were loss of righting reflex, tremors, clonic convulsions, paralysis of hind limbs, and coma.

11 DESCRIPTION

Argatroban is a synthetic direct thrombin inhibitor and the chemical name is 1-[5-[(aminoiminomethyl)amino]-1-oxo-2-[[(1,2,3,4-tetrahydro-3-methyl-8- quinolinyl)sulfonyl]amino]pentyl]-4-methyl-2-piperidinecarboxylic acid, monohydrate. Argatroban has 4 asymmetric carbons. One of the asymmetric carbons has an R configuration (stereoisomer Type I) and an S configuration (stereoisomer Type II). Argatroban consists of a mixture of R and S stereoisomers at a ratio of approximately 65:35.

The molecular formula of argatroban is C23H36N6O5S•H2O. Its molecular weight is 526.66 g/mol. The structural formula is shown below:

Argatroban is a white, odorless crystalline powder that is freely soluble in glacial acetic acid, slightly soluble in ethanol, and insoluble in acetone, ethyl acetate, and ether.

Argatroban Injection 250 mg/2.5 mL (100 mg/mL) is a sterile clear, colorless to pale yellow, slightly viscous solution. Argatroban Injection 250 mg/2.5 mL (100 mg/mL) is available in 250-mg (in 2.5-mL) single-dose amber vials, with white flip-top caps. Each mL of sterile, nonpyrogenic solution contains 100 mg Argatroban. Inert ingredients (per vial): 1300 mg Propylene glycol, 760 mg Dehydrated alcohol.

12 CLINICAL PHARMACOLOGY

12.1 Mechanism of Action

Argatroban is a direct thrombin inhibitor that reversibly binds to the thrombin active site. Argatroban does not require the co-factor antithrombin III for antithrombotic activity. Argatroban exerts its anticoagulant effects by inhibiting thrombin-catalyzed or -induced reactions, including fibrin formation; activation of coagulation factors V, VIII, and XIII; activation of protein C; and platelet aggregation.

Argatroban inhibits thrombin with an inhibition constant (Ki) of 0.04 μM. At therapeutic concentrations, argatroban has little or no effect on related serine proteases (trypsin, factor Xa, plasmin, and kallikrein).

Argatroban is capable of inhibiting the action of both free and clot-associated thrombin.

12.2 Pharmacodynamics

When argatroban is administered by continuous infusion, anticoagulant effects and plasma concentrations of argatroban follow similar, predictable temporal response profiles, with low intersubject variability. Immediately upon initiation of argatroban infusion, anticoagulant effects are produced as plasma argatroban concentrations begin to rise. Steady-state levels of both drug and anticoagulant effect are typically attained within 1 to 3 hours and are maintained until the infusion is discontinued or the dosage adjusted. Steady-state plasma argatroban concentrations increase proportionally with dose (for infusion doses up to 40 mcg/kg/min in healthy subjects) and are well correlated with steady-state anticoagulant effects. For infusion doses up to 40 mcg/kg/min, argatroban increases in a dose-dependent fashion, the aPTT, ACT, the prothrombin time (PT), the International Normalized Ratio (INR), and the thrombin time (TT) in healthy volunteers and cardiac patients. Representative steady-state plasma argatroban concentrations and anticoagulant effects are shown below for argatroban infusion doses up to 10 mcg/kg/min (see Figure 1).

Figure 1. Relationship at Steady State Between Argatroban Dose, Plasma Argatroban Concentration and Anticoagulant Effect

Effect on International Normalized Ratio (INR): Because argatroban is a direct thrombin inhibitor, co-administration of argatroban and warfarin produces a combined effect on the laboratory measurement of the INR. However, concurrent therapy, compared to warfarin monotherapy, exerts no additional effect on vitamin K–dependent factor Xa activity.

The relationship between INR on co-therapy and warfarin alone is dependent on both the dose of argatroban and the thromboplastin reagent used. This relationship is influenced by the International Sensitivity Index (ISI) of the thromboplastin. Data for 2 commonly utilized thromboplastins with ISI values of 0.88 (Innovin, Dade) and 1.78 (Thromboplastin C Plus, Dade) are presented in Figure 2 for an argatroban dose of 2 mcg/kg/min. Thromboplastins with higher ISI values than shown result in higher INRs on combined therapy of warfarin and argatroban. These data are based on results obtained in normal individuals [see Drug Interactions (7.2), Dosage and Administration (2.5), Warnings and Precautions (5.3)].

Figure 2. INR Relationship of Argatroban Plus Warfarin Versus Warfarin Alone

Figure 2 demonstrates the relationship between INR for warfarin alone and INR for warfarin co-administered with argatroban at a dose of 2 mcg/kg/min. To calculate INR for warfarin alone (INRW), based on INR for co-therapy of warfarin and argatroban (INRWA), when the argatroban dose is 2 mcg/kg/min, use the equation next to the appropriate curve. Example: At a dose of 2 mcg/kg/min and an INR performed with Thromboplastin A, the equation 0.19 + 0.57 (INRWA) = INRW would allow a prediction of the INR on warfarin alone (INRW). Thus, using an INRWA value of 4.0 obtained on combined therapy: INRW = 0.19 + 0.57 (4) = 2.47 as the value for INR on warfarin alone. The error (confidence interval) associated with a prediction is ± 0.4 units. Similar linear relationships and prediction errors exist for argatroban at a dose of 1 mcg/kg/min. Thus, for argatroban doses of 1 or 2 mcg/kg/min, INRW can be predicted from INRWA. For argatroban doses greater than 2 mcg/kg/min, the error associated with predicting INRW from INRWA is ± 1. Thus, INRW cannot be reliably predicted from INRWA at doses greater than 2 mcg/kg/min.

12.3 Pharmacokinetics

Distribution
Argatroban distributes mainly in the extracellular fluid as evidenced by an apparent steady-state volume of distribution of 174 mL/kg (12.18 L in a 70 kg adult). Argatroban is 54% bound to human serum proteins, with binding to albumin and α1-acid glycoprotein being 20% and 34%, respectively.

Metabolism
The main route of argatroban metabolism is hydroxylation and aromatization of the 3-methyltetrahydroquinoline ring in the liver. The formation of each of the 4 known metabolites is catalyzed in vitro by the human liver microsomal cytochrome P450 enzymes CYP3A4/5. The primary metabolite (M1) exerts 3- to 5-fold weaker anticoagulant effects than argatroban. Unchanged argatroban is the major component in plasma. The plasma concentrations of M1 range between 0% and 20% of that of the parent drug. The other metabolites (M2 to M4) are found only in very low quantities in the urine and have not been detected in plasma or feces. These data, together with the lack of effect of erythromycin (a potent CYP3A4/5 inhibitor) on argatroban pharmacokinetics, suggest that CYP3A4/5-mediated metabolism is not an important elimination pathway in vivo.

Total body clearance is approximately 5.1 mL/kg/min (0.31 L/kg/hr) for infusion doses up to 40 mcg/kg/min. The terminal elimination half-life of argatroban ranges between 39 and 51 minutes.

There is no interconversion of the 21–(R):21–(S) diastereoisomers. The plasma ratio of these diastereoisomers is unchanged by metabolism or hepatic impairment, remaining constant at 65:35 (± 2%).

Excretion
Argatroban is excreted primarily in the feces, presumably through biliary secretion. In a study in which ^14C-argatroban (5 mcg/kg/min) was infused for 4 hours into healthy subjects, approximately 65% of the radioactivity was recovered in the feces within 6 days of the start of infusion with little or no radioactivity subsequently detected. Approximately 22% of the radioactivity appeared in the urine within 12 hours of the start of infusion. Little or no additional urinary radioactivity was subsequently detected. Average percent recovery of unchanged drug, relative to total dose, was 16% in urine and at least 14% in feces.

Special Populations
Hepatic Impairment: The dosage of argatroban should be decreased in patients with hepatic impairment [see Dosage and Administration (2.4), Warnings and Precautions (5.2)]. Patients with hepatic impairment were not studied in percutaneous coronary intervention (PCI) trials. At a dose of 2.5 mcg/kg/min, hepatic impairment is associated with decreased clearance and increased elimination half-life of argatroban (to 1.9 mL/kg/min and 181 minutes, respectively, for patients with a Child-Pugh score greater than 6).

Renal Impairment: No dosage adjustment is necessary in patients with renal dysfunction. The effect of renal disease on the pharmacokinetics of argatroban was studied in 6 subjects with normal renal function (mean Clcr = 95 ± 16 mL/min) and in 18 subjects with mild (mean Clcr = 64 ± 10 mL/min), moderate (mean Clcr = 41 ± 5.8 mL/min), and severe (mean Clcr = 5 ± 7 mL/min) renal impairment. The pharmacokinetics and pharmacodynamics of argatroban at dosages up to 5 mcg/kg/min were not significantly affected by renal dysfunction.

Use of argatroban was evaluated in a study of 12 patients with stable end-stage renal disease undergoing chronic intermittent hemodialysis. Argatroban was administered at a rate of 2 to 3 mcg/kg/min (begun at least 4 hours prior to dialysis) or as a bolus dose of 250 mcg/kg at the start of dialysis followed by a continuous infusion of 2 mcg/kg/min. Although these regimens did not achieve the goal of maintaining ACT values at 1.8 times the baseline value throughout most of the hemodialysis period, the hemodialysis sessions were successfully completed with both of these regimens. The mean ACTs produced in this study ranged from 1.39 to 1.82 times baseline, and the mean aPTTs ranged from 1.96 to 3.4 times the baseline. When argatroban was administered as a continuous infusion of 2 mcg/kg/min prior to and during a 4-hour hemodialysis session, approximately 20% was cleared through dialysis.

Age, Gender: There are no clinically significant effects of age or gender on the pharmacokinetics or pharmacodynamics (e.g., aPTT) of argatroban in adults.

Drug-Drug Interactions

Digoxin: In 12 healthy volunteers, intravenous infusion of argatroban (2 mcg/kg/min) over 5 days (study days 11 to 15) did not affect the steady-state pharmacokinetics of oral digoxin (0.375 mg daily for 15 days).

Erythromycin: In 10 healthy subjects, orally administered erythromycin (a potent inhibitor of CYP3A4/5) at 500 mg four times daily for 7 days had no effect on the pharmacokinetics of argatroban at a dose of 1 mcg/kg/min for 5 hours. These data suggest oxidative metabolism by CYP3A4/5 is not an important elimination pathway in vivo for argatroban.

Aspirin and Acetaminophen: Drug-drug interactions have not been demonstrated between argatroban and concomitantly administered aspirin (162.5 mg orally given 26 and 2 hours prior to initiation of argatroban 1 mcg/kg/min over 4 hours) or acetaminophen (1,000 mg orally given 12, 6, and 0 hours prior to, and 6 and 12 hours subsequent to, initiation of argatroban 1.5 mcg/kg/min over 18 hours).

13 NONCLINICAL TOXICOLOGY

13.1 Carcinogenesis, Mutagenesis, Impairment of Fertility

Carcinogenicity studies with argatroban have not been performed.

Argatroban was not genotoxic in the Ames test, the Chinese hamster ovary cell (CHO/HGPRT) forward mutation test, the Chinese hamster lung fibroblast chromosome aberration test, the rat hepatocyte, and WI-38 human fetal lung cell unscheduled DNA synthesis (UDS) tests, or the mouse micronucleus test.

Argatroban at intravenous doses up to 27 mg/kg/day (0.3 times the recommended maximum human dose based on body surface area) had no effect on fertility and reproductive function of male and female rats.

14 CLINICAL STUDIES

14.1 Heparin-Induced Thrombocytopenia

The safety and efficacy of argatroban were evaluated in a historically controlled efficacy and safety study (Study 1) and a follow-on efficacy and safety study (Study 2). These studies were comparable with regard to study design, study objectives, dosing regimens as well as study outline, conduct, and monitoring. In these studies, 568 adult patients were treated with argatroban and 193 adult patients made up the historical control group. Patients had a clinical diagnosis of heparin-induced thrombocytopenia, either without thrombosis (HIT) or with thrombosis (HITTS [heparin-induced thrombocytopenia and thrombosis syndrome]) and were males or non-pregnant females between the age of 18 and 80 years old. HIT/HITTS was defined by a fall in platelet count to less than 100,000/μL or a 50% decrease in platelets after the initiation of heparin therapy with no apparent explanation other than HIT. Patients with HITTS also had an arterial or venous thrombosis documented by appropriate imaging techniques or supported by clinical evidence such as acute myocardial infarction, stroke, pulmonary embolism, or other clinical indications of vascular occlusion. Patients who had documented histories of positive heparin-dependent antibody tests without current thrombocytopenia or heparin challenge (e.g., patients with latent disease) were also included if they required anticoagulation.

These studies did not include patients with documented unexplained aPTT >200% of control at baseline, documented coagulation disorder or bleeding diathesis unrelated to HIT, a lumbar puncture within the past 7 days or a history of previous aneurysm, hemorrhagic stroke, or a thrombotic stroke within the past 6 months unrelated to HIT.

The initial dose of argatroban was 2 mcg/kg/min. Two hours after the start of the argatroban infusion, an aPTT level was obtained and dose adjustments were made (up to a maximum of 10 mcg/kg/min) to achieve a steady-state aPTT value that was 1.5 to 3.0 times the baseline value, not to exceed 100 seconds. Overall the mean aPTT level for HIT and HITTS patients during the argatroban infusion increased from baseline values of 34 and 38 seconds, respectively, to 62.5 and 64.5 seconds, respectively.

The primary efficacy analysis was based on a comparison of event rates for a composite endpoint that included death (all causes), amputation (all causes) or new thrombosis during the treatment and follow-up period (study days 0 to 37). Secondary analyses included evaluation of the event rates for the components of the composite endpoint as well as time-to-event analyses.

In Study 1, a total of 304 patients were enrolled as follows: active HIT (n = 129), active HITTS (n =144), or latent disease (n = 31). Among the 193 historical controls, 139 (72%) had active HIT, 46 (24%) had active HITTS, and 8 (4%) had latent disease. Within each group, those with active HIT and those with latent disease were analyzed together. Positive laboratory confirmation of HIT/HITTS by the heparin-induced platelet aggregation test or serotonin release assay was demonstrated in 174 of 304 (57%) argatroban-treated patients (i.e., in 80 with HIT or latent disease and 94 with HITTS) and in 149 of 193 (77%) historical controls (i.e., in 119 with HIT or latent disease and 30 with HITTS). The test results for the remainder of the patients and controls were either negative or not determined.

There was a significant improvement in the composite outcome in patients with HIT and HITTS treated with argatroban versus those in the historical control group (see Table 9). The components of the composite endpoint are shown in Table 9.

Table 9
Efficacy Results of Study 1: Composite Endpointa and Individual Components, Ranked by Severityb
Parameter, N (%) | HIT |  |  | HITTS |  | HIT/HITTS
Parameter, N (%) | Control n = 147 | Argatroban n = 160 |  | Control n = 46 | Argatroban n = 144 | Control n = 193 | Argatroban n = 304
Composite Endpoint | 57 (38.8) | 41 (25.6) |  | 26 (56.5) | 63 (43.8) | 83 (43.0) | 104 (34.2)
Individual Componentsb
Death | 32 (21.8) | 27 (16.9) | 13 (28.3) |  | 26 (18.1) | 45 (23.3) | 53 (17.4)
Amputation | 3 (2.0) | 3 (1.9) | 4 (8.7) |  | 16 (11.1) | 7 (3.6) | 19 (6.2)
New Thrombosis | 22 (15.0) | 11 (6.9) | 9 (19.6) |  | 21 (14.6) | 31 (16.1) | 32 (10.5)

a) Death (all cause), amputation (all cause), or new thrombosis within 37-day study period.
b) Reported as the most severe outcome among the components of composite endpoint (severity ranking: death > amputation > new thrombosis); patients may have had multiple outcomes.

Time-to-event analyses showed significant improvements in the time-to-first event in patients with HIT or HITTS treated with argatroban versus those in the historical control group. The between-group differences in the proportion of patients who remained free of death, amputation, or new thrombosis were statistically significant in favor of argatroban by these analyses.

A time-to-event analysis for the composite endpoint is shown in Figure 3 for patients with HIT and Figure 4 for patients with HITTS.

Figure 3. Time to First Event for the Composite Efficacy Endpoint: HIT Patients

* Censored indicates no clinical endpoint (defined as death, amputation, or new thrombosis) was observed during the follow-up period (maximum period of follow-up was 37 days).

Figure 4. Time to First Event for the Composite Efficacy Endpoint: HITTS Patients

* Censored indicates no clinical endpoint (defined as death, amputation, or new thrombosis) was observed during the follow-up period (maximum period of follow-up was 37 days).

In Study 2, a total of 264 patients were enrolled as follows: HIT (n = 125) or HITTS (n = 139). There was a significant improvement in the composite efficacy outcome for argatroban-treated patients, versus the same historical control group from Study 1, among patients having HIT (25.6% vs. 38.8%), patients having HITTS (41.0% vs. 56.5%), and patients having either HIT or HITTS (33.7% vs. 43.0%). Time-to-event analyses showed significant improvements in the time-to-first event in patients with HIT or HITTS treated with argatroban versus those in the historical control group. The between-group differences in the proportion of patients who remained free of death, amputation, or new thrombosis were statistically significant in favor of argatroban.

Anticoagulant Effect
In Study 1, the mean (± SE) dose of argatroban administered was 2.0 ± 0.1 mcg/kg/min in the HIT arm and 1.9 ± 0.1 mcg/kg/min in the HITTS arm. Seventy-six percent of patients with HIT and 81% of patients with HITTS achieved a target aPTT at least 1.5-fold greater than the baseline aPTT at the first assessment occurring on average at 4.6 hours (HIT) and 3.9 hours (HITTS) following initiation of argatroban therapy.

No enhancement of aPTT response was observed in subjects receiving repeated administration of argatroban.

Platelet Count Recovery
In Study 1, 53% of patients with HIT and 58% of patients with HITTS, had a recovery of platelet count by Day 3. Platelet Count Recovery was defined as an increase in platelet count to >100,000/μL or to at least 1.5-fold greater than the baseline count (platelet count at study initiation) by Day 3 of the study.

14.2 Percutaneous Coronary Intervention (PCI) Patients with or at Risk for HIT

In 3 similarly designed trials, argatroban was administered to 91 patients with current or previous clinical diagnosis of HIT or heparin-dependent antibodies, who underwent a total of 112 percutaneous coronary interventions (PCIs) including percutaneous transluminal coronary angioplasty (PTCA), coronary stent placement, or atherectomy. Among the 91 patients undergoing their first PCI with argatroban, notable ongoing or recent medical history included myocardial infarction (n = 35), unstable angina (n = 23), and chronic angina (n = 34). There were 33 females and 58 males. The average age was 67.6 years (median 70.7, range 44 to 86), and the average weight was 82.5 kg (median 81.0 kg, range 49 to 141).

Twenty-one of the 91 patients had a repeat PCI using argatroban an average of 150 days after their initial PCI. Seven of 91 patients received glycoprotein IIb/IIIa inhibitors. Safety and efficacy were assessed against historical control populations who had been anticoagulated with heparin.

All patients received oral aspirin (325 mg) 2 to 24 hours prior to the interventional procedure. After venous or arterial sheaths were in place, anticoagulation was initiated with a bolus of argatroban of 350 mcg/kg via a large-bore intravenous line or through the venous sheath over 3 to 5 minutes. Simultaneously, a maintenance infusion of 25 mcg/kg/min was initiated to achieve a therapeutic ACT of 300 to 450 seconds. If necessary to achieve this therapeutic range, the maintenance infusion dose was titrated (15 to 40 mcg/kg/min) and/or an additional bolus dose of 150 mcg/kg could be given. Each patient’s ACT was checked 5 to 10 minutes following the bolus dose. The ACT was checked as clinically indicated. Arterial and venous sheaths were removed no sooner than 2 hours after discontinuation of argatroban and when the ACT was less than 160 seconds.

If a patient required anticoagulation after the procedure, argatroban could be continued, but at a lower infusion dose between 2.5 and 5 mcg/kg/min. An aPTT was drawn 2 hours after this dose reduction and the dose of argatroban then was adjusted as clinically indicated (not to exceed 10 mcg/kg/min), to reach an aPTT between 1.5 and 3 times baseline value (not to exceed 100 seconds).

In 92 of the 112 interventions (82%), the patient received the initial bolus of 350 mcg/kg and an initial infusion dose of 25 mcg/kg/min. The majority of patients did not require additional bolus dosing during the PCI procedure. The mean value for the initial ACT measurement after the start of dosing for all interventions was 379 sec (median 338 sec; 5th percentile-95th percentile 238 to 675 sec). The mean ACT value per intervention over all measurements taken during the procedure was 416 sec (median 390 sec; 5th percentile-95th percentile 261 to 698 sec). About 65% of patients had ACTs within the recommended range of 300 to 450 seconds throughout the procedure. The investigators did not achieve anticoagulation within the recommended range in about 23% of patients. However, in this small sample, patients with ACTs below 300 seconds did not have more coronary thrombotic events, and patients with ACTs over 450 seconds did not have higher bleeding rates.

Acute procedural success was defined as lack of death, emergent coronary artery bypass graft (CABG), or Q-wave myocardial infarction. Acute procedural success was reported in 98.2% of patients who underwent PCIs with argatroban anticoagulation compared with 94.3% of historical control patients anticoagulated with heparin (p = NS). Among the 112 interventions, 2 patients had emergency CABGs, 3 had repeat PTCAs, 4 had non-Q-wave myocardial infarctions, 3 had myocardial ischemia, 1 had an abrupt closure, and 1 had an impending closure (some patients may have experienced more than 1 event). No patients died.

16 HOW SUPPLIED/STORAGE AND HANDLING

Argatroban Injection is available as follows:

NDC Strength Packaged

0143-9288-01 250 mg/2.5 mL (100 mg/mL) Single Dose Vial

Storage and Handling

Store the vials in original carton at 20° to 25° C (68° to 77° F) [See USP Controlled Room Temperature]. Do not freeze. Retain in the original carton to protect from light. If the solution is cloudy, or if an insoluble precipitate is noted, the vial should be discarded.

17 PATIENT COUNSELING INFORMATION

Inform patients of the risks associated with Argatroban Injection as well as the plan for regular monitoring during administration of the drug. Specifically, inform patients to report:

- the use of any other products known to affect bleeding.
- any medical history that may increase the risk for bleeding, including a history of severe hypertension; recent lumbar puncture or spinal anesthesia; major surgery, especially involving the brain, spinal cord, or eye; hematologic conditions associated with increased bleeding tendencies such as congenital or acquired bleeding disorders and gastrointestinal lesions such as ulcerations.
- any bleeding signs or symptoms
- the occurrence of any signs or symptoms of allergic reactions (e.g., airway reactions, skin reactions and vasodilation reactions)

PREMIERProRx®

Manufactured by:
Exela Pharma Sciences, LLC
Lenoir, NC 28645

Distributed by:
Hikma Pharmaceuticals USA Inc.
Berkeley Heights, NJ 07922

PREMIERProRx® is a registered trademark of Premier Healthcare Alliance, L.P., used under license.

October 2020

PRINCIPAL DISPLAY PANEL

NDC 0143-9288-01
Argatroban
Injection
250 mg/2.5 mL
(100 mg/mL) Rx ONLY
DILUTE PRIOR TO ADMINISTRATION
For Intravenous Infusion Only
Single-Use Vial
Discard Unused Portion

Single-Use Vial NDC 0143-9288-01
Discard Unused Portion
Argatroban
Injection
250 mg/2.5 mL
(100 mg/mL)
DILUTE PRIOR TO ADMINISTRATION
For Intravenous Infusion Only
Rx ONLY
PREMIERProRx®